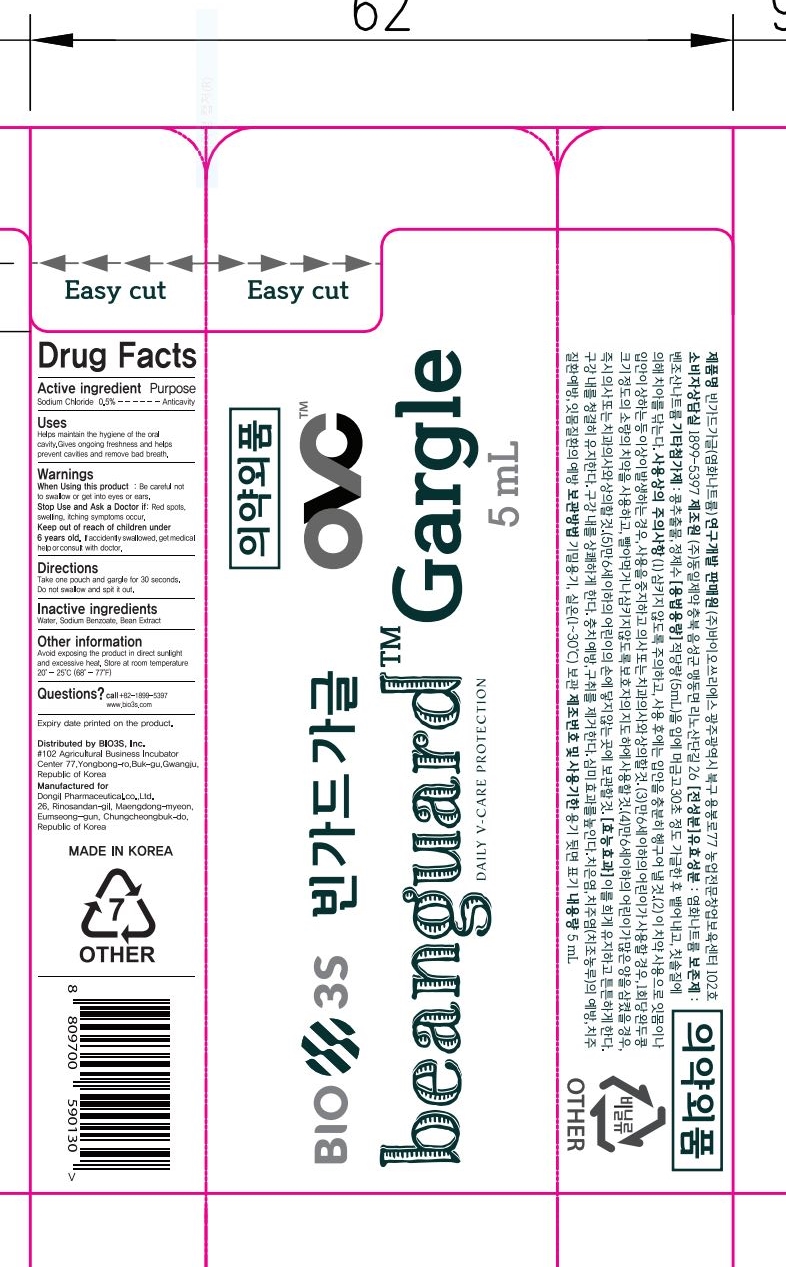 DRUG LABEL: Beanguard Gargle
NDC: 77935-302 | Form: LIQUID
Manufacturer: BIO3S Co.,Ltd.
Category: otc | Type: HUMAN OTC DRUG LABEL
Date: 20211008

ACTIVE INGREDIENTS: SODIUM CHLORIDE 0.5 g/100 mL
INACTIVE INGREDIENTS: BEAN; WATER; SODIUM BENZOATE

77935-302 Beanguard Gargle

Active Ingredients

Sodium Chloride 0.5%

Purpose

Anticavity

Uses

Helps maintain the hygiene of the oral
cavity.Gives ongoing freshness and helps
prevent cavities with removing bad breath.

Warnings

Do not swallow.

Warnings

Keep out of reach of children under 6 years old.

If accidently swallowed, get medical help or consult with doctor

Warnings

Stop Use and Ask a Doctor if : red spots, swelling, itching symptoms occur.

Warnings

When Using this product : Be careful not to swallow or get into eyes or ears.

Inactive Ingredients

water, sodium benzoate, bean extract

Directions

Take one pouch and gargle for 30 seconds.
Do not swallow and spit it out

Other Information

Avoid exposing the product in direct sunlight
and excessive heat. Store at room temperature
20°-25°C (68°-77°F

Warnings

If accidently swallowed, get medical help or consult with doctor.